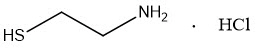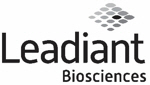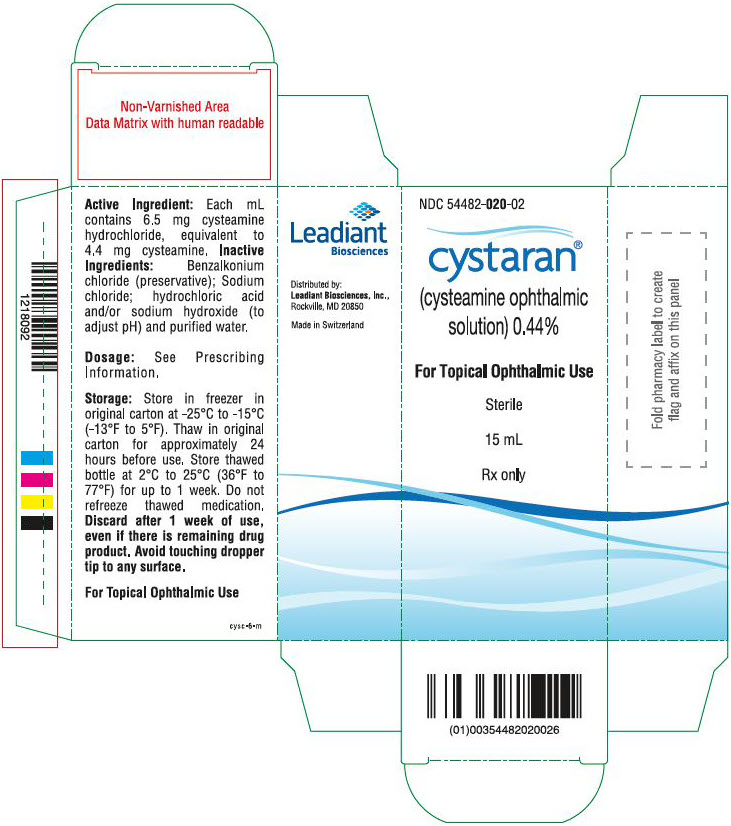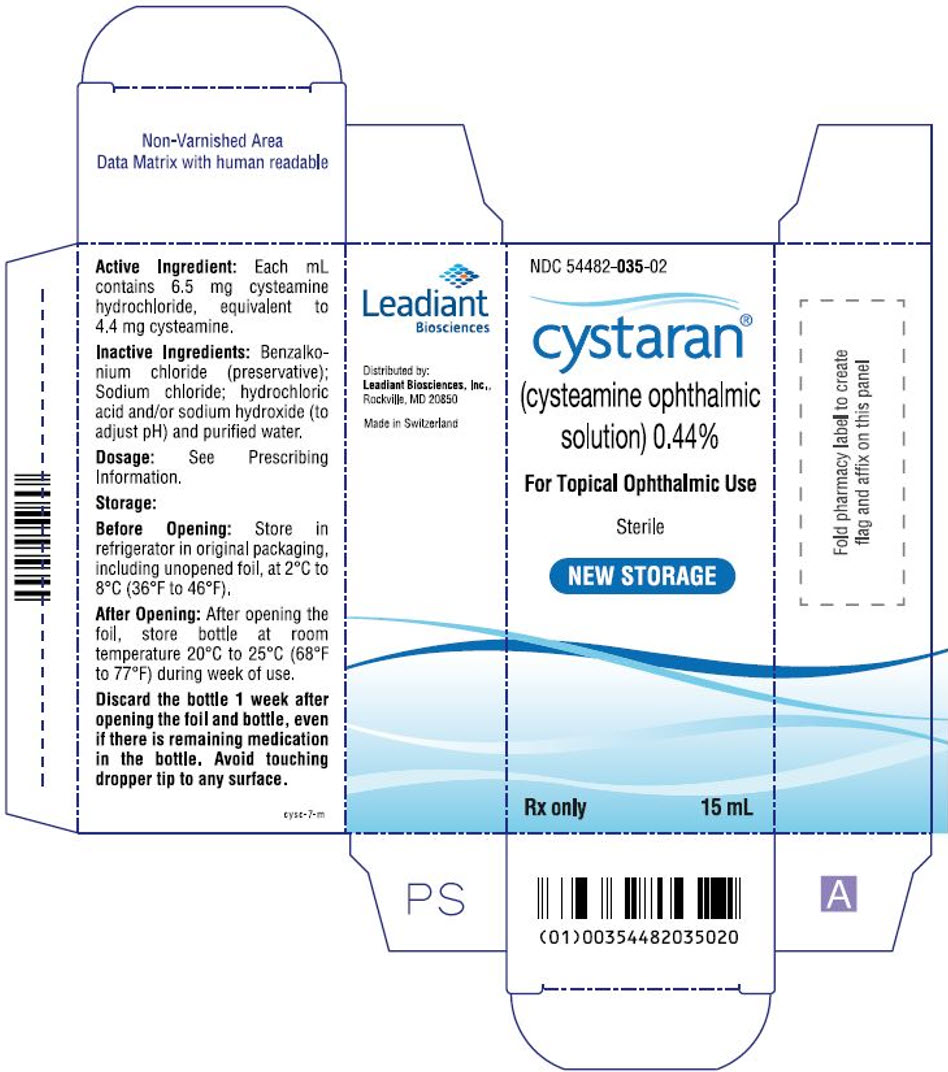 DRUG LABEL: CYSTARAN
NDC: 54482-020 | Form: SOLUTION
Manufacturer: Leadiant Biosciences, Inc.
Category: prescription | Type: HUMAN PRESCRIPTION DRUG LABEL
Date: 20250430

ACTIVE INGREDIENTS: CYSTEAMINE HYDROCHLORIDE 6.5 mg/1 mL
INACTIVE INGREDIENTS: BENZALKONIUM CHLORIDE; SODIUM CHLORIDE; HYDROCHLORIC ACID; SODIUM HYDROXIDE; WATER

HIGHLIGHTS OF PRESCRIBING INFORMATION

These highlights do not include all the information needed to use CYSTARAN® safely and effectively. See full prescribing information for CYSTARAN.
CYSTARAN (cysteamine ophthalmic solution) 0.44%, for topical ophthalmic use
Initial U.S. Approval: 1994

1 INDICATIONS AND USAGE

CYSTARAN is a cystine-depleting agent indicated for the treatment of corneal cystine crystal accumulation in patients with cystinosis. (1)

2 DOSAGE AND ADMINISTRATION

Instill one drop of CYSTARAN in each eye, every waking hour. (2)

3 DOSAGE FORMS AND STRENGTHS

Ophthalmic solution containing 6.5 mg/mL of cysteamine hydrochloride equivalent to 4.4 mg/mL of cysteamine (0.44%). (3)

4 CONTRAINDICATIONS

None. (4)

5 WARNINGS AND PRECAUTIONS

To minimize the risk of contamination, do not touch the dropper tip to any surface. Keep bottle tightly closed when not in use. (5.1)

6 ADVERSE REACTIONS

The most common adverse reactions (incidence approximately 10% or greater) are sensitivity to light, redness, eye pain/irritation, headache and visual field defects. (6)

To report SUSPECTED ADVERSE REACTIONS, contact Leadiant Biosciences, Inc. at 1-888-393-4584 or FDA at 1-800-FDA-1088 or www.fda.gov/medwatch.

FULL PRESCRIBING INFORMATION

1 INDICATIONS AND USAGE

CYSTARAN® is a cystine-depleting agent indicated for the treatment of corneal cystine crystal accumulation in patients with cystinosis.

2 DOSAGE AND ADMINISTRATION

Instill one drop of CYSTARAN in each eye, every waking hour.

Do not touch dropper tip to any surface, as this may contaminate the solution.

Discard after 1 week of use.

3 DOSAGE FORMS AND STRENGTHS

Ophthalmic solution containing 6.5 mg/mL of cysteamine hydrochloride equivalent to 4.4 mg/mL of cysteamine (0.44%).

4 CONTRAINDICATIONS

None.

5 WARNINGS AND PRECAUTIONS

5.1 Contamination of Tip and Solution

To minimize contaminating the dropper tip and solution, care should be taken not to touch the eyelids or surrounding areas with the dropper tip of the bottle. Keep bottle tightly closed when not in use.

5.2 Benign Intracranial Hypertension

There have been reports of benign intracranial hypertension (or pseudotumor cerebri) associated with oral cysteamine treatment that has resolved with the addition of diuretic therapy.

There have also been reports associated with ophthalmic use of cysteamine; however, all of these patients were on concurrent oral cysteamine.

5.3 Contact Lens Use

CYSTARAN contains benzalkonium chloride, which may be absorbed by soft contact lenses. Contact lenses should be removed prior to application of solution and may be reinserted 15 minutes following its administration [see Patient Counseling Information (17)].

5.4 Topical Ophthalmic Use

CYSTARAN is for topical ophthalmic use.

6 ADVERSE REACTIONS

6.1 Clinical Trials Experience

Because clinical trials are conducted under widely varying conditions, adverse reaction rates observed in the clinical trials of a drug cannot be directly compared to rates in the clinical trials of another drug and may not reflect the rates observed in practice.

The safety data described below reflect exposure in controlled clinical trials of six months to 19 years duration in approximately 300 patients.

The most frequently reported ocular adverse reactions occurring in ≥10% of patients were sensitivity to light, redness, and eye pain/irritation, headache and visual field defects.

8 USE IN SPECIFIC POPULATIONS

8.1 Pregnancy

Risk Summary

There are no adequate and well controlled studies of ophthalmic cysteamine in pregnant women to inform any drug associated risks. Oral administration of cysteamine to pregnant rats throughout the period of organogenesis was teratogenic at doses 86 to 345 times the recommended human ophthalmic dose (based on body surface area) [see Data]. CYSTARAN should be used during pregnancy only if the potential benefit justifies the potential risk to the fetus.

Data

Animal Data

Teratology studies have been performed in rats at oral doses in the range of 37.5 mg/kg/day to 150 mg/kg/day (86 to 345 times the recommended human ophthalmic dose based on a body surface area) and have revealed cysteamine bitartrate to be teratogenic. Observed teratogenic findings were intrauterine death, cleft palate, kyphosis, heart ventricular septal defects, microcephaly, exencephaly, and growth deficits.

8.2 Lactation

Risk Summary

There is no information regarding the presence of cysteamine in human milk, the effects on the breastfed infants, or the effects on milk production. Cysteamine administered orally is present in milk of lactating rats. It is not known whether measurable levels of cysteamine would be present in maternal milk following topical ocular administration of CYSTARAN.

8.4 Pediatric Use

The safety and effectiveness of CYSTARAN (cysteamine ophthalmic solution) 0.44% have been established in pediatric patients.

8.5 Geriatric Use

When the clinical studies with CYSTARAN were conducted, the reduced life expectancy from cystinosis did not make it possible to include patients in the geriatric age range.

8.6 Renal Impairment

The effect of renal impairment on the pharmacokinetics of cysteamine following ophthalmic administration of cysteamine ophthalmic solution has not been evaluated because ophthalmic exposure compared to systemic exposure is negligible. The majority of the patients in the ophthalmic clinical studies are assumed to have had some degree of renal impairment due to their underlying systemic disease. The total daily ophthalmic dose is less than 2% of the recommended oral daily dose of cysteamine; thus, the systemic exposure following ophthalmic administration is expected to be negligible compared to oral administration.

11 DESCRIPTION

CYSTARAN is a sterile ophthalmic solution containing 6.5 mg/mL of cysteamine hydrochloride, equivalent to 4.4 mg/mL of cysteamine (0.44%) as the active ingredient. Cysteamine is a cystine-depleting agent which lowers the cystine content of cells in patients with cystinosis.

Molecular Formula: C2H7NS HCl
Molecular Weight: 113.61

Each milliliter of CYSTARAN contains: Active: cysteamine 4.4 mg (equivalent to cysteamine hydrochloride 6.5 mg); Preservative: benzalkonium chloride 0.1 mg; Inactive Ingredients: sodium chloride, hydrochloric acid and/or sodium hydroxide (to adjust pH to 4.1-4.5), and purified water.

12 CLINICAL PHARMACOLOGY

12.1 Mechanism of Action

Cysteamine acts as a cystine-depleting agent by converting cystine to cysteine and cysteine-cysteamine mixed disulfides and reduces corneal cystine crystal accumulation.

12.3 Pharmacokinetics

The peak plasma concentration of cysteamine following ocular administration of cysteamine ophthalmic solution in humans is unknown, but it is expected to be substantially less than the peak plasma concentration following oral administration of cysteamine bitartrate.

13 NONCLINICAL TOXICOLOGY

13.1 Carcinogenesis, Mutagenesis, Impairment of Fertility

Carcinogenesis

Cysteamine has not been tested for its carcinogenic potential in long-term animal studies.

Mutagenesis

Cysteamine was not mutagenic in the Ames test. It produced a negative response in an in vitro sister chromatid exchange assay in human lymphocytes but a positive response in a similar assay in hamster ovarian cells.

Impairment of Fertility

Repeat breeding reproduction studies were conducted in male and female rats. Cysteamine was found to have no effect on fertility and reproductive performance at an oral dose of 75 mg/kg/day (173 times the recommended human ophthalmic dose based on body surface area). At an oral dose of 375 mg/kg/day (864 times the recommended human ophthalmic dose based on body surface area), it reduced the fertility of the adult rats and the survival of their offspring.

14 CLINICAL STUDIES

Clinical efficacy was evaluated in controlled clinical trials in approximately 300 patients. The primary efficacy end point was the response rate of eyes that had a reduction of at least 1 unit in the photo-rated Corneal Cystine Crystal Score (CCCS) at some time point during the study when baseline CCCS ≥1, or a lack of an increase of more than 1 unit in CCCS throughout the study when baseline CCCS <1.

Study 1 combined the data from three smaller studies. For eyes with a lower baseline of CCCS <1, the response rate was 13% (4/30) [95% CI: (4, 32)]. For eyes with a higher baseline of CCCS ≥1, the response rate was 32% (94/291) [95% CI: (27, 38)].

Study 2 evaluated ocular cystinosis patients who had a baseline of CCCS ≥1. The response rate was 67% (10/15) [95% CI: (38, 88)].

Study 3 also evaluated ocular cystinosis patients; for eyes with a baseline of CCCS ≥1, the response rate was 33% (3/9) [95% CI: (8, 70)].

Corneal crystals accumulate if CYSTARAN is discontinued.

16 HOW SUPPLIED/STORAGE AND HANDLING

Fifteen (15) mL of CYSTARAN (cysteamine ophthalmic solution) 0.44% is supplied in an opaque, white, low-density polyethylene (LDPE) 88 mm tall bottle with a 1.6 mm blue, silicone rubber flow-controlled dropper tip and closed with a white, high-density polyethylene (HDPE) screw cap. The bottle is foil-wrapped and stored in a carton.

STORAGE AND HANDLING

CYSTARAN bottles must be stored in the following conditions:

NDC 54482-020-02

Before Opening: Store unopened bottle in freezer at -25°C to -15°C (-13°F to 5°F) in the original packaging including unopened foil. Thaw for approximately 24 hours before use.
Open the carton and the foil only when starting a new bottle.
After Opening: Record discard date on the bottle, which is 1 week from the day the foil and bottle were opened. Store thawed bottle at 2°C to 25°C (36°F to 77°F) for up to 1 week. The thawed bottle does not require refrigeration between use. Do not refreeze the thawed medication. Discard 1 week after the foil and bottle were opened even if there is medication left in the bottle.

NDC 54482-035-02

Before Opening: Store unopened bottle in refrigerator at 2°C to 8°C (36°F to 46°F) in the original packaging including unopened foil.
Open the carton and the foil only when starting a new bottle.
After Opening: Record discard date on the bottle, which is 1 week from the day the foil and bottle were opened. During the week of use, store bottle at room temperature, 20°C to 25°C (68°F to 77°F). Discard 1 week after the foil and bottle were opened even if there is medication left in the bottle.

17 PATIENT COUNSELING INFORMATION

Storage of Cystaran Bottles NDC 54482-020-02

1. Patients should be advised to store unopened bottles in the freezer in the intact foil pouch and original carton.
2. Each week, one new bottle should be removed from the freezer.
3. Patients should be advised to allow the bottle to thaw completely (approximately 24 hours) prior to use.
4. After the bottle is completely thawed, the patient should be advised to open the packaging (carton and foil) and record the discard date on the bottle label. The discard date is seven (7) days from the day the foil and bottle were opened.
5. During the week of use, patients should be advised to store thawed bottle at 2°C to 25°C (36°F to 77°F) for up to 1 week. The thawed bottle does not require refrigeration between use and should not be refrozen.
6. At the end of 1 week (7 days), patients should discard the bottle. There may be medication left in the bottle; however, the bottle must be discarded by the patient because the medication is only stable for 1 week after the foil and bottle were opened.

Storage of Cystaran Bottles NDC 54482-035-02

1. Patients should be advised to store unopened bottles in the refrigerator in the intact foil pouch and original carton.
2. When starting a new bottle, patients should be advised to open the packaging (carton and foil) and record the discard date on the bottle label. The discard date is seven (7) days from the day the foil and bottle were opened.
3. During the week of use, patients should be advised to store the bottle at room temperature 20°C to 25°C (68°F to 77°F) for up to 1 week.
4. At the end of 1 week (7 days), patients should discard the bottle. There may be medication left in the bottle; however, the bottle must be discarded by the patient because the medication is only stable for 1 week after the foil and bottle were opened.

Risk of Contamination

Patients should be advised not to touch the eyelid or surrounding areas with the dropper tip of the bottle. The cap should remain on the bottle when not in use.

Use with Contact Lenses

Patients should be advised that contact lenses should be removed prior to application of CYSTARAN. Contact lenses may be reinserted 15 minutes following CYSTARAN administration.

Topical Ophthalmic Use

Patients should be advised that CYSTARAN is for topical ophthalmic use.

CYSTARAN (cysteamine ophthalmic solution) 0.44% is distributed by Leadiant Biosciences, Inc., Rockville, MD 20850.

cyspi-6-m

PRINCIPAL DISPLAY PANEL - 15 mL Bottle Carton

NDC 54482-020-02

cystaran®

(cysteamine ophthalmic
solution) 0.44%

For Topical Ophthalmic Use

Sterile

15 mL

Rx only

Active Ingredient: Each mL
contains 6.5 mg cysteamine
hydrochloride, equivalent to
4.4 mg cysteamine. Inactive
Ingredients: Benzalkonium
chloride (preservative); Sodium
chloride; hydrochloric acid
and/or sodium hydroxide (to
adjust pH) and purified water.

Dosage: See Prescribing
Information.

Storage: Store in freezer in
original carton at -25°C to -15°C
(-13°F to 5°F). Thaw in original
carton for approximately 24
hours before use. Store thawed
bottle at 2°C to 25°C (36°F to
77°F) for up to 1 week. Do not
refreeze thawed medication.
Discard after 1 week of use,
even if there is remaining drug
product. Avoid touching dropper
tip to any surface.

For Topical Ophthalmic Use

cysc-6-m

Distributed by:
Leadiant Biosciences Inc.,
Rockville, MD 20850

Made in Switzerland

PRINCIPAL DISPLAY PANEL - Carton

NDC 54482-035-02

cystaran®
(cysteamine ophthalmic
solution) 0.44%

For Topical Ophthalmic Use

Sterile

NEW STORAGE

Rx only

15 mL

Active Ingredient: Each mL
contains 6.5 mg cysteamine
hydrochloride, equivalent to
4.4 mg cysteamine.

Inactive Ingredients: Benzalko-
nium chloride (preservative);
Sodium chloride; hydrochloric
acid and/or sodium hydroxide (to
adjust pH) and purified water.

Dosage: See Prescribing
Information.

Storage:

Before Opening: Store in
refrigerator in original packaging,
including unopened foil, at 2°C to
8°C (36°F to 46°F).

After Opening: After opening the
foil, store bottle at room
temperature 20°C to 25°C (68°F
to 77°F) during week of use.

Discard the bottle 1 week after
opening the foil and bottle, even
if there is remaining medication
in the bottle. Avoid touching
dropper tip to any surface.

cysc-7-m

Distributed by:
Leadiant Biosciences, Inc.,
Rockville, MD 20850

Made in Switzerland